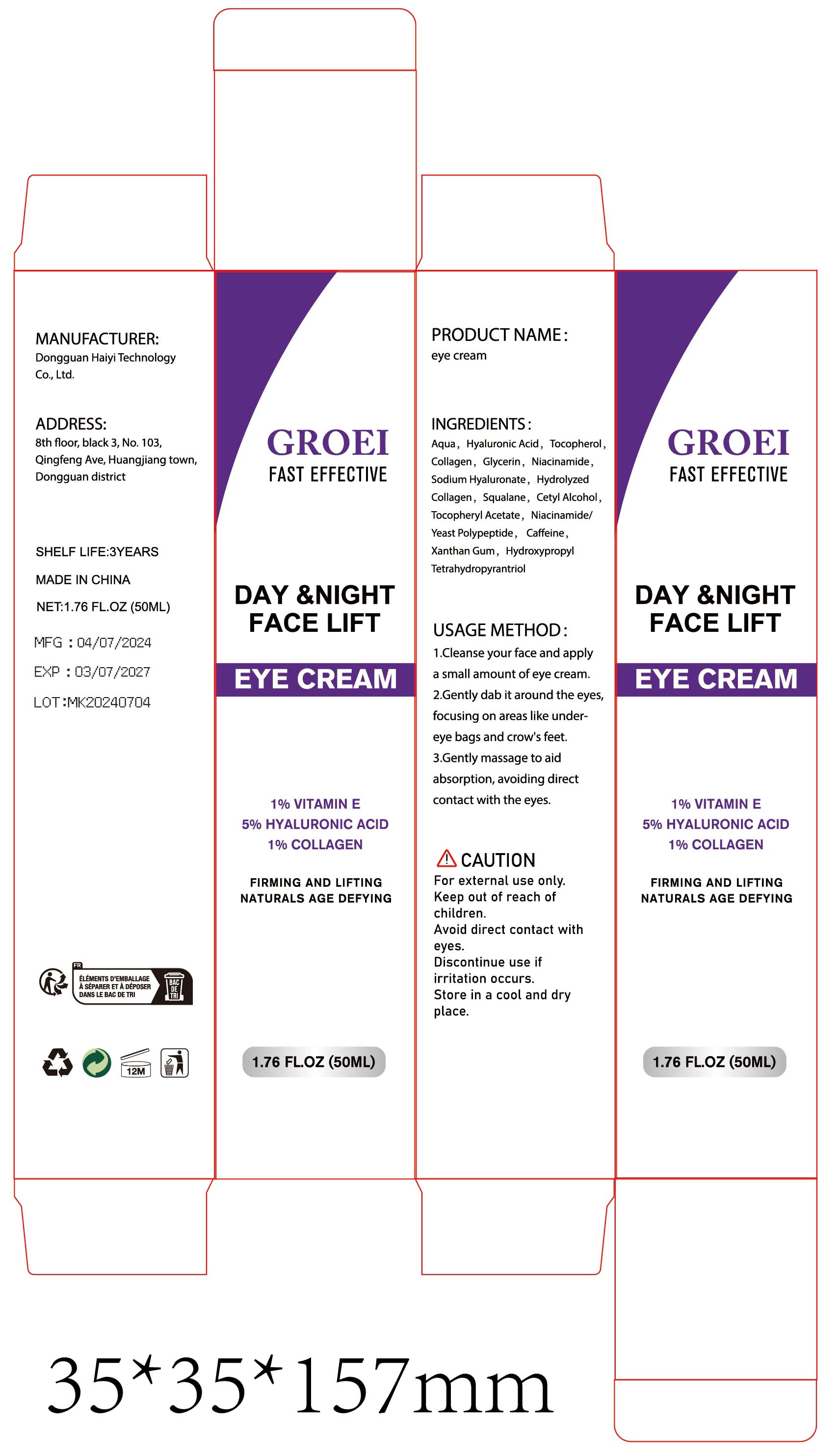 DRUG LABEL: eye Cream
NDC: 84732-084 | Form: CREAM
Manufacturer: Dongguan Haiyi Technology Co.,Ltd.
Category: otc | Type: HUMAN OTC DRUG LABEL
Date: 20241105

ACTIVE INGREDIENTS: HYALURONIC ACID 5 mg/100 mL; TOCOPHEROL 1 mg/100 mL; COLLAGEN ALPHA-1(I) CHAIN BOVINE 1 mg/100 mL
INACTIVE INGREDIENTS: WATER; NIACINAMIDE; .ALPHA.-TOCOPHEROL ACETATE; CAFFEINE; CETYL ALCOHOL; HYDROXYPROPYL TETRAHYDROPYRANTRIOL; SQUALANE; XANTHAN GUM; GLYCERIN; SODIUM HYALURONATE

Active ingredient

1% VITAMIN E

5% HYALURONIC ACID

1% COLLAGEN

Inactive ingredient

Aqua, Tocopherol.Collagen, Glycerin, Niacinamide,Sodium Hyaluronate, Hydrolyzed Collagen, Squalane, Cetyl Alcohol,Tocopheryl Acetate, Niacinamide/Yeast Polypeptide, Caffeine,Xanthan Gum, Hydroxypropyl Tetrahydropyrantriol

Purpose section

FIRMING AND LIFTING

NATURALS AGE DEFYING

Warning

1).For external use only, avoid directcontact with eyes, lf you feel any
discomfort, stop using itand wash it with plenty of water. In severe cases,
pleaseseek medical attention in time.
2). Not allowed to be used ondamaged skin,

stop use

This product may cause allergic reactions in asmall number of people.
lf youexperience any discomfort,please stop using it immediately.

not use

Not suitable for use by children, pregnantor breast feeding people.

OUT OF CHILDREN

KEEP THE PRODUCT OUT OF REACH OF CHILDREN to

HOW TO USE

1.Cleanse your face and applya small amount of eye cream.

2.Gently dab it around the eyes,focusing on areas like under-eye bags and crow's feet.

3.Gently massage to aidabsorption, avoiding directcontact with the eyes.

Dosage

take an appropriateamount,Use 2-3 times a week